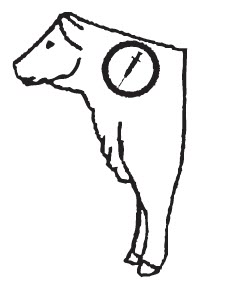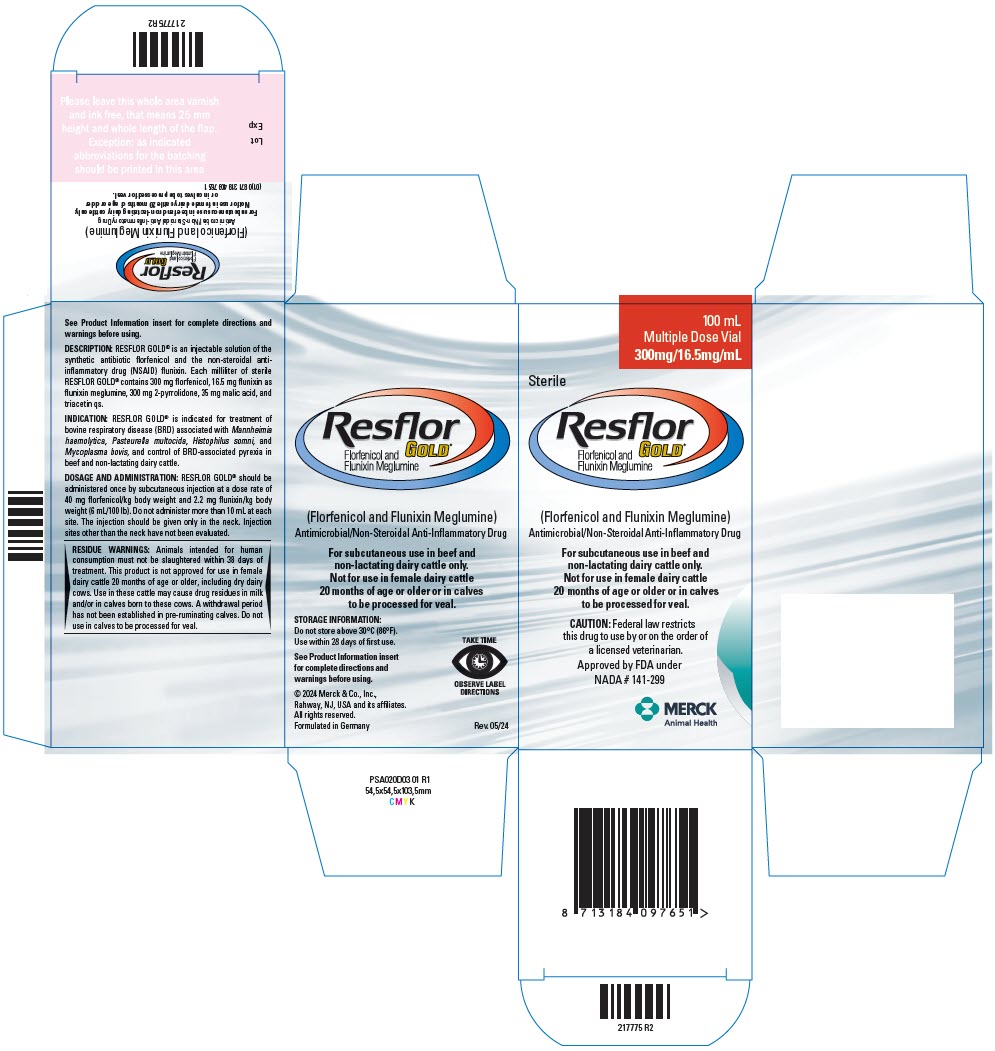 DRUG LABEL: Resflor Gold
NDC: 0061-4305 | Form: INJECTION
Manufacturer: Merck Sharp & Dohme Corp.
Category: animal | Type: PRESCRIPTION ANIMAL DRUG LABEL
Date: 20241119

ACTIVE INGREDIENTS: FLORFENICOL 300 mg/1 mL; FLUNIXIN MEGLUMINE 16.5 mg/1 mL

Resflor
GOLD®

(Florfenicol and Flunixin Meglumine)
Antimicrobial/Non-Steroidal Anti-Inflammatory Drug

For subcutaneous use in beef and non-lactating dairy cattle only.

Not for use in female dairy cattle 20 months of age or older or in calves to be processed for veal.

PRODUCT INFORMATION

CAUTION: Federal law restricts this drug to use by or on the order of a licensed veterinarian.

DESCRIPTION

DESCRIPTION: RESFLOR GOLD® is an injectable solution of the synthetic antibiotic florfenicol and the non-steroidal anti-inflammatory drug (NSAID) flunixin. Each milliliter of sterile RESFLOR GOLD® contains 300 mg florfenicol, 16.5 mg flunixin as flunixin meglumine, 300 mg 2-pyrrolidone, 35 mg malic acid, and triacetin qs.

INDICATIONS AND USAGE

INDICATION: RESFLOR GOLD® is indicated for treatment of bovine respiratory disease (BRD) associated with Mannheimia haemolytica, Pasteurella multocida, Histophilus somni, and Mycoplasma bovis, and control of BRD-associated pyrexia in beef and non-lactating dairy cattle.

DOSAGE AND ADMINISTRATION: RESFLOR GOLD® should be administered once by subcutaneous injection at a dose rate of 40 mg florfenicol/kg body weight and 2.2 mg flunixin/kg body weight (6 mL/100 lb). Do not administer more than 10 mL at each site. The injection should be given only in the neck. Injection sites other than the neck have not been evaluated. For the 500 mL vial, do not puncture the stopper more than 20 times.

RESFLOR GOLD® Dosage Guide [Do not administer more than 10 mL at each site.]
ANIMAL WEIGHT (lbs) | DOSAGE (mL)
100 | 6.0 | Recommended Injection Location
200 | 12.0 | Recommended Injection Location
300 | 18.0 | Recommended Injection Location
400 | 24.0 | Recommended Injection Location
500 | 30.0 | Recommended Injection Location
600 | 36.0 | Recommended Injection Location
700 | 42.0 | Recommended Injection Location
800 | 48.0 | Recommended Injection Location
900 | 54.0 | Recommended Injection Location
1000 | 60.0 | Recommended Injection Location

CONTRAINDICATIONS

CONTRAINDICATIONS: Do not use in animals that have shown hypersensitivity to florfenicol or flunixin.

WARNINGS

WARNINGS: NOT FOR HUMAN USE. KEEP OUT OF REACH OF CHILDREN. This product contains material that can be irritating to skin and eyes. Avoid direct contact with skin, eyes, and clothing. In case of accidental eye exposure, flush with water for 15 minutes. In case of accidental skin exposure, wash with soap and water. Remove contaminated clothing. Consult a physician if irritation persists. Accidental injection of this product may cause local irritation. Consult a physician immediately. The Safety Data Sheet (SDS) contains more detailed occupational safety information.

For customer service, adverse effects reporting, and/or a copy of the SDS, call 1-800-211-3573. For additional information about adverse drug experience reporting for animal drugs, contact FDA at 1-888-FDAVETS, or http://www.fda.gov/reportanimalae.

PRECAUTIONS

PRECAUTIONS: As a class, cyclo-oxygenase inhibitory NSAIDs may be associated with gastrointestinal, renal, and hepatic toxicity. Sensitivity to drug-associated adverse events varies with the individual patient. Patients at greatest risk for adverse events are those that are dehydrated, on diuretic therapy, or those with existing renal, cardiovascular, and/or hepatic dysfunction. Concurrent administration of potentially nephrotoxic drugs should be carefully monitored. NSAIDs may inhibit the prostaglandins that maintain normal homeostatic function. Such anti-prostaglandin effects may result in clinically significant disease in patients with underlying or pre-existing disease that have not been previously diagnosed. Since many NSAIDs possess the potential to produce gastrointestinal ulceration, concomitant use of RESFLOR GOLD® with other anti-inflammatory drugs, such as NSAIDs or corticosteroids, should be avoided or closely monitored.

Flunixin is a cyclo-oxygenase inhibitory NSAID, and as with others in this class, adverse effects may occur with its use. The most frequently reported adverse effects have been gastrointestinal signs. Events involving suspected renal, hematologic, neurologic, dermatologic, and hepatic effects have also been reported for other drugs in this class.

Not for use in animals intended for breeding purposes. The effects of RESFLOR GOLD® on bovine reproductive performance, pregnancy, and lactation have not been determined. Toxicity studies in dogs, rats, and mice have associated the use of florfenicol with testicular degeneration and atrophy. NSAIDs are known to have potential effects on both parturition and the estrous cycle. There may be a delay in the onset of estrus if flunixin is administered during the prostaglandin phase of the estrous cycle. Studies have associated the use of flunixin in cattle with a delay in parturition and prolonged labor (which may increase the risk of stillbirth), and interference with involution and expulsion of fetal membranes (which may increase the risk for placental retention and metritis).

RESFLOR GOLD®, when administered as directed, may induce a transient reaction at the site of injection and underlying tissues that may result in trim loss of edible tissue at slaughter.

RESIDUE WARNING

RESIDUE WARNINGS: Animals intended for human consumption must not be slaughtered within 38 days of treatment. This product is not approved for use in female dairy cattle 20 months of age or older, including dry dairy cows. Use in these cattle may cause drug residues in milk and/or in calves born to these cows. A withdrawal period has not been established in preruminating calves. Do not use in calves to be processed for veal.

ADVERSE REACTIONS

ADVERSE REACTIONS: Transient inappetence, diarrhea, decreased water consumption, and injection site swelling have been associated with the use of florfenicol in cattle. In addition, anaphylaxis and collapse have been reported post-approval with the use of another formulation of florfenicol in cattle.

In cattle, rare instances of anaphylactic-like reactions, some of which have been fatal, have been reported, primarily following intravenous use of flunixin meglumine.

CLINICAL PHARMACOLOGY:

The pharmacokinetics (PK) of florfenicol (Table 1) and flunixin (Table 2) after subcutaneous injection of RESFLOR GOLD® is described below:

Table 1. Mean (n=28) pharmacokinetic parameters for florfenicol in cattle after a single subcutaneous administration of RESFLOR GOLD (florfenicol dose of 40 mg/kg BW).
Mean Florfenicol PK parameters in Cattle
PK Parameter | AUC0-t (ng*hr/mL) | AUC0-inf (ng*hr/mL) | Cmax (ng/mL) | Tmax (hr) | T½ (hr) | MRT0-inf (hr)
Mean | 242527 | 247577 | 11151 | 6.25 | 28.5 | 27.3
SD | 42741 | 41391 | 4194 | 3.87 | 9.91 | 11.6

Table 2. Mean (n=28) pharmacokinetic parameters for flunixin in cattle after a single subcutaneous administration of RESFLOR GOLD (flunixin dose of 2.2 mg/kg BW).
Mean Flunixin PK parameters in Cattle
PK Parameter | AUC0-t [AUC0-t = Area under the plasma-concentration-time curve (AUC) from time zero to the last quantifiable concentrations] (ng*hr/mL) | AUC0-inf [AUC0-inf = AUC from time zero to infinity] (ng*hr/mL) | Cmax [Cmax = Maximum plasma concentration] (ng/mL) | Tmax [Tmax = Time at which Cmax was observed] (hr) | T½ [T½ = Terminal elimination half-life] (hr) | MRT0-inf [MRT0-inf = Mean residence time from time zero to infinity] (hr)
Mean | 13370 | 14448 [n=27] | 1913 | 1.14 | 9.5 | 11.4
SD [SD = Standard deviation] | 4964 | 5116 | 791 | 0.97 | 3.27 | 4.41

MICROBIOLOGY

MICROBIOLOGY: Florfenicol is a synthetic, broad-spectrum antibiotic active against many Gram-negative and Gram-positive bacteria isolated from domestic animals. It acts by binding to the 50S ribosomal subunit and inhibiting bacterial protein synthesis. Florfenicol is generally considered a bacteriostatic drug, but exhibits bactericidal activity against certain bacterial species.

In vitro studies demonstrate that florfenicol is active against the BRD pathogens M. haemolytica, P. multocida, and H. somni, and M. bovis that florfenicol exhibits bactericidal activity against strains of M. haemolytica and H. somni.

The minimum inhibitory concentrations (MICs) of florfenicol were determined for non-mycoplasmal BRD isolates obtained from calves enrolled in BRD field studies in the U.S. in 2006 using methods recommended by the Clinical and Laboratory Standards Institute (M31-A2). MICs for M. bovis isolates were determined by an accepted method using Hayflick Broth with Alamar Blue (HBAN) medium under appropriate control. Isolates were obtained from pre-treatment nasal swabs from all calves enrolled at all four sites, post-treatment nasal swabs from treatment failures in the RESFLOR GOLD and saline control treatment groups at three sites, and lung tissue from one calf that died in the saline control treatment group. The results are shown in belowTable 3.

Table 3. Florfenicol MIC values [The correlation between in vitro susceptibility data and clinical effectiveness is unknown.] of indicated pathogens isolated from cattle with naturally-ocurring BRD.
Indicated pathogens | Year of isolation | Number of isolates | MIC50 [The lowest MIC to encompass 50% and 90% of the most susceptible isolates, respectively.] (μg/mL) | MIC90 (μg/mL) | MIC range (μg/mL)
Mannheimia haemolytica | 2006 | 183 | 1.0 | 1.0 | 0.5 to 32
Pasteurella multocida | 2006 | 139 | 0.5 | 0.5 | ≤ 0.125 to 16
Histophilus somni | 2006 | 84 | ≤ 0.125 | ≤ 0.125 | ≤ 0.125 to 0.25
Mycoplasma bovis | 2006 | 60 | 1.0 | 1.0 | 0.5 to 1.0

EFFECTIVENESS: In a multi-site field study, calves with naturally-occurring BRD were treated with RESFLOR GOLD®, Nuflor Gold® (NADA 141-265), or saline. A treatment success was defined as a calf with normal respiration to mild respiratory distress, normal attitude to mildly depressed, and a rectal temperature < 104.0 °F on Day 11.

The treatment success rate for BRD for the RESFLOR GOLD® treatment group (68.4%) was statistically significantly greater (p = 0.0255) compared to the saline control treatment group (42.9%). RESFLOR GOLD® was non-inferior to Nuflor Gold® for the treatment of BRD, with a one-sided 95% lower confidence bound for the difference between the two treatments equal to -13.2%.

In the same study, the change in rectal temperature from pre-treatment to six hours post-treatment was evaluated to determine the effectiveness of RESFLOR GOLD® for the control of BRD-associated pyrexia. The proportion of calves whose rectal temperatures decreased by ≥ 2.0 °F from pre-treatment to six hours post-treatment was statistically significantly greater (p = 0.0019) in the RESFLOR GOLD® treatment group compared to the saline control treatment group. The mean decrease in rectal temperature from pre-treatment to six hours post-treatment was statistically significantly greater in the RESFLOR GOLD® treatment group compared to the Nuflor Gold® and saline control treatment groups (p = 0.0031 and 0.0002, respectively).

The effectiveness of RESFLOR GOLD for the treatment of BRD associated with Mycoplasma bovis was demonstrated by examining the M. bovis data from cattle enrolled in the BRD treatment study described above. There were numerically more treatment successes (6 of 8 calves, 75%) than treatment failures (2 of 8 calves, 25%) in RESFLOR GOLD-treated calves that cultured positive for M. bovis pre-treatment.

FOOD SAFETY WARNING

ANIMAL SAFETY: A target animal safety study was conducted to evaluate the effects of RESFLOR GOLD® when administered to cattle subcutaneously at 1X, 3X, or 5X the labeled dose for three consecutive days (3X the labeled duration). Decreased feed and water consumption, and decreased body weights (secondary to decreased feed consumption) were observed in the 1X, 3X, and 5X groups. Injection site swellings were noted in the 1X, 3X, and 5X groups.

A separate injection site study was conducted in cattle. The study demonstrated that RESFLOR GOLD®, when administered according to the label directions, may induce a transient local reaction in the subcutaneous and underlying muscle tissue.

STORAGE AND HANDLING

STORAGE INFORMATION: Do not store above 30°C (86°F). Use within 28 days of first use.

HOW SUPPLIED

HOW SUPPLIED: RESFLOR GOLD® is available in 100, 250, and 500 mL sterile, multiple-dose, glass vials.

Formulated in Germany
Intervet Inc. (d/b/a Merck Animal Health)
126 E. Lincoln Ave., Rahway, NJ, 07065
Copyright © 2024 Merck & Co., Inc.,
Rahway, NJ, USA and its affiliates. All rights reserved
Rev. 05/24

Approved by FDA under NADA # 141-299
217772 R3

PRINCIPAL DISPLAY PANEL - 100 mL Vial Carton

100 mL
Multiple Dose Vial
300mg/16.5mg/mL

Sterile

Resflor
GOLD®
Florfenicol and
Flunixin Meglumine

(Florfenicol and Flunixin Meglumine)
Antimicrobial/Non-Steroidal Anti-Inflammatory Drug

For subcutaneous use in beef and
non-lactating dairy cattle only.
Not for use in female dairy cattle
20 months of age or older or in calves
to be processed for veal.

CAUTION: Federal law restricts
this drug to use by or on the order of
a licensed veterinarian.

Approved by FDA under
NADA # 141-299

MERCK
Animal Health